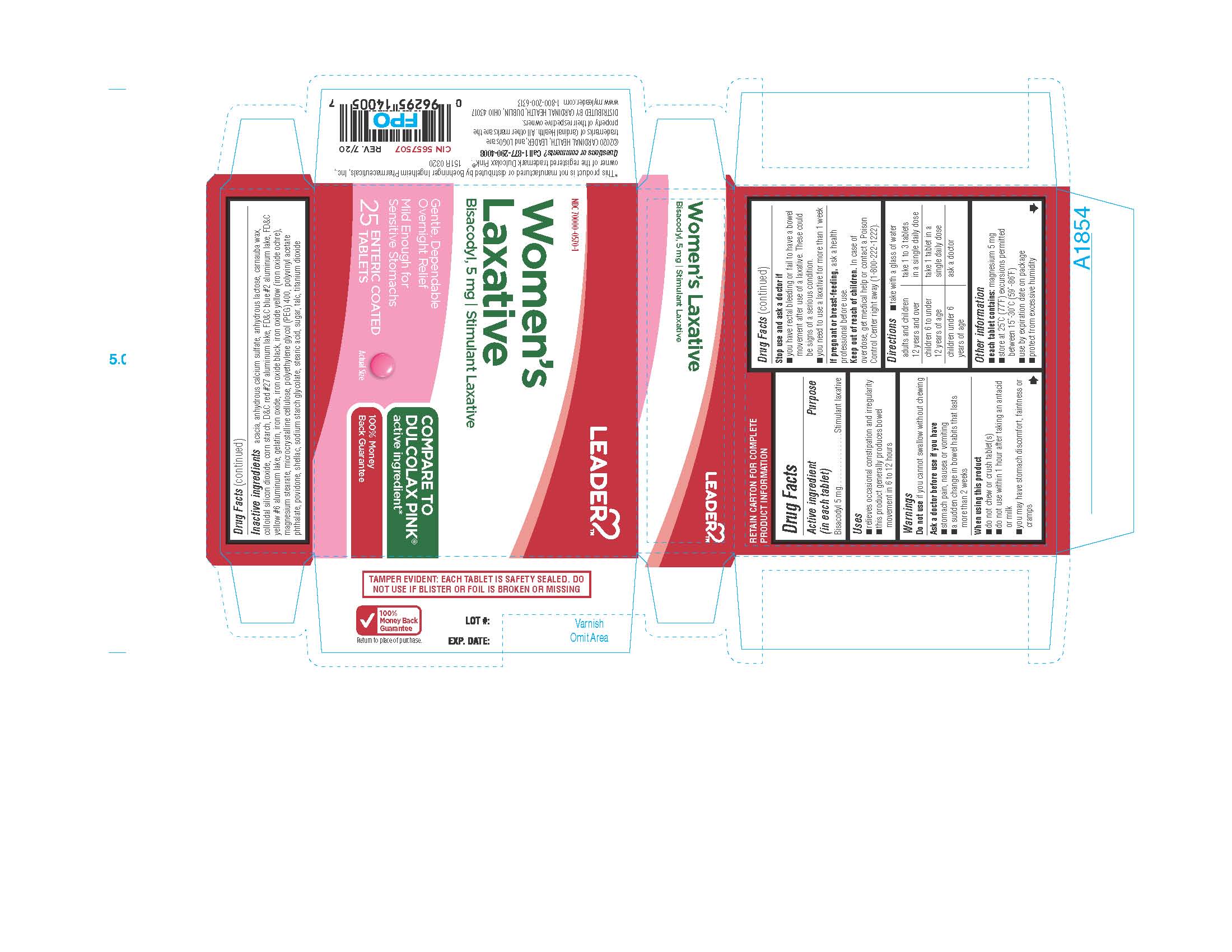 DRUG LABEL: WOMENS LAXATIVE ENTERIC COATED
NDC: 70000-0570 | Form: TABLET, COATED
Manufacturer: CARDINAL HEALTH
Category: otc | Type: HUMAN OTC DRUG LABEL
Date: 20240111

ACTIVE INGREDIENTS: BISACODYL 5 mg/1 1
INACTIVE INGREDIENTS: FD&C BLUE NO. 2; FERRIC OXIDE YELLOW; MAGNESIUM STEARATE; POLYETHYLENE GLYCOL 400; POVIDONE; SODIUM STARCH GLYCOLATE TYPE A CORN; POLYVINYL ACETATE PHTHALATE; RAW SUGAR; ACACIA; FERROSOFERRIC OXIDE; STEARIC ACID; ANHYDROUS LACTOSE; CARNAUBA WAX; STARCH, CORN; D&C RED NO. 27; FD&C YELLOW NO. 6; GELATIN; FERROUS OXIDE; CALCIUM SULFATE ANHYDROUS; SILICON DIOXIDE; MICROCRYSTALLINE CELLULOSE; SHELLAC; TALC; TITANIUM DIOXIDE

LEADER-CARDINAL 151R 25 COUNT BLISTERS

ACTIVE INGREDIENT

In each tablet: Bisacodyl 5mg

PURPOSE

Stimulant Laxative

INDICATIONS AND USAGE

- relieves occasional constipation and irregularity
- this product generally produces bowel movement in 6 to 12 hours

Warnings

Do not useif you cannot swallow without chewing

Ask a doctor before use if you have

- stomach pain, nausea or vomiting
- a sudden change in bowel habits that lasts more than two weeks

When using this product

- do not chew or crush tablet(s)
- do not use within 1 hour after taking an antacid or milk
- you may have stomach discomfort, faintness or cramps

Stop use and ask a doctor if

- you have rectal bleeding or fail to have a bowel movement after use of a laxative. These could be signs of a serious condition.
- you need to use a laxative for more than 1 week

PREGNANCY OR BREAST FEEDING

If pregnant or breast-feeding,ask a health professional before use.

Keep out of reach of children.In case of overdose, get medical help or contact a Poison Control Center right away (1-800-222-1222).

DOSAGE AND ADMINISTRATION

- take with a glass of water

adults and children 12 years and over take 1 to 3 tablets in a single daily dose

children 6 to under 12 years of age take 1 tablet in a single daily dose

children under 6 years of age ask a doctor

Other Information

- each tablet contains:magnesium 5mg
- store at 25°C (77F) excursions permitted between 15° - 30°C (59° - 86°F)
- use by expiration date on package
  - protect from excessive humidity

INACTIVE INGREDIENTS

Acacia, Anhydrous Calcium Sulfate, Anhydrous Lactose, Carnauba Wax, Colloidal Silicon Dioxide, Corn Starch, D&C Red #27 Aluminum Lake, FD&C Blue #2 Aluminum Lake, FD&C Yellow #6 Aluminum Lake, Gelatin, Iron Oxide, Iron Oxide Black, Iron Oxide Yellow (Iron Oxide Ochre), Magnesium Stearate,Microcrystalline Cellulose, Polyethylene Glycol (PEG) 400, Polyvinyl Acetate Phthalate, Povidone,Shellac, Sodium Starch Glycolate, Stearic Acid, Sugar, Talc, Titanium Dioxide